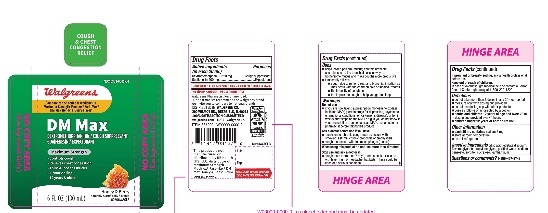 DRUG LABEL: Mucus Relief DM Honey and Berry Flavor
NDC: 0363-6005 | Form: SOLUTION
Manufacturer: WALGREENS CO.
Category: otc | Type: HUMAN OTC DRUG LABEL
Date: 20251125

ACTIVE INGREDIENTS: DEXTROMETHORPHAN HYDROBROMIDE 20 mg/20 mL; GUAIFENESIN 400 mg/20 mL
INACTIVE INGREDIENTS: ANHYDROUS CITRIC ACID; EDETATE DISODIUM; PROPYLENE GLYCOL; WATER; SODIUM BENZOATE; SORBITOL; SUCRALOSE; XANTHAN GUM

Walgreen Mucus Relief DM Honey & Berry Flavor

Drug Facts

ACTIVE INGREDIENT

PURPOSE

Active ingredients (in each 20 mL) | Purposes
Dextromethorphan HBr 20 mg | Cough suppressant
Guaifenesin 400 mg | Expectorant

Uses

- helps loosen phlegm (mucus) and thin bronchial secretions to rid the bronchial passageways of bothersome mucus and make coughs more productive
- temporarily relieves:
  - cough due to minor throat and bronchial irritation as may occur with the common cold or inhaled irritants
  - the intensity of coughing
  - the impulse to cough to help you get to sleep

Warnings

Do not use

- if you are now taking a prescription monoamine oxidase inhibitor (MAOI) (certain drugs for depression, psychiatric, or emotional conditions, or Parkinson's disease), or for 2 weeks after stopping the MAOI drug. If you do not know if your prescription drug contains an MAOI, ask a doctor or pharmacist before taking this product.

Ask a doctor before use if you have

- persistent or chronic cough such as occurs with smoking, asthma, chronic bronchitis, or emphysema
- cough that occurs with too much phlegm (mucus)

When using this product do not use more than directed

Stop use and ask a doctor if

- cough lasts more than 7 days, comes back, or occurs with fever, rash, or headache that lasts. These could be signs of a serious condition.

PREGNANCY OR BREAST FEEDING

If pregnant or breast-feeding,ask a health professional before use.

Keep out of reach of children.

In case of overdose, get medical help or contact a Poison Control Center right away at 1-800-222-1222.

Directions

- do not take more than 6 doses in any 24-hour period
- measure only with dosing cup provided
- do not use dosing cup with other products
- dose as follows or as directed by a doctor
- adults and children 12 years of age and over:20 mL in dosing cup provided every 4 hours
- children under 12 years of age:do not use

Other information

- each 20 mL contains: sodium 12 mg
- store at room temperature
- do not refrigerate

Inactive ingredients

citric acid, edetate disodium, flavors, glycerin, propylene glycol, purified water, sodium benzoate, sorbitol, sucralose, xanthan gum

Questions?

1-866-467-2748)

Dist. by:

PRINCIPAL DISPLAY PANEL - 180 mL Bottle Label

*Compare to the active ingredient in Maximum Strength Mucinex® Fast Max® DM Max Honey & Berry Flavour

NDC 0363-6005-06

Mucus

Relief DM

Dextromethorphan HBr – Cough Suppressant

Guaifenesin – Expectorant

Maximum Strength

- Controls Cough
- Relieves Chest Congestion
- Thins & Loosens Mucus
- 4 Hour Dosing

Honey& Berry Flavor

Naturally and Artificially Flavored

For Ages 12+

6 FL OZ (180mL)